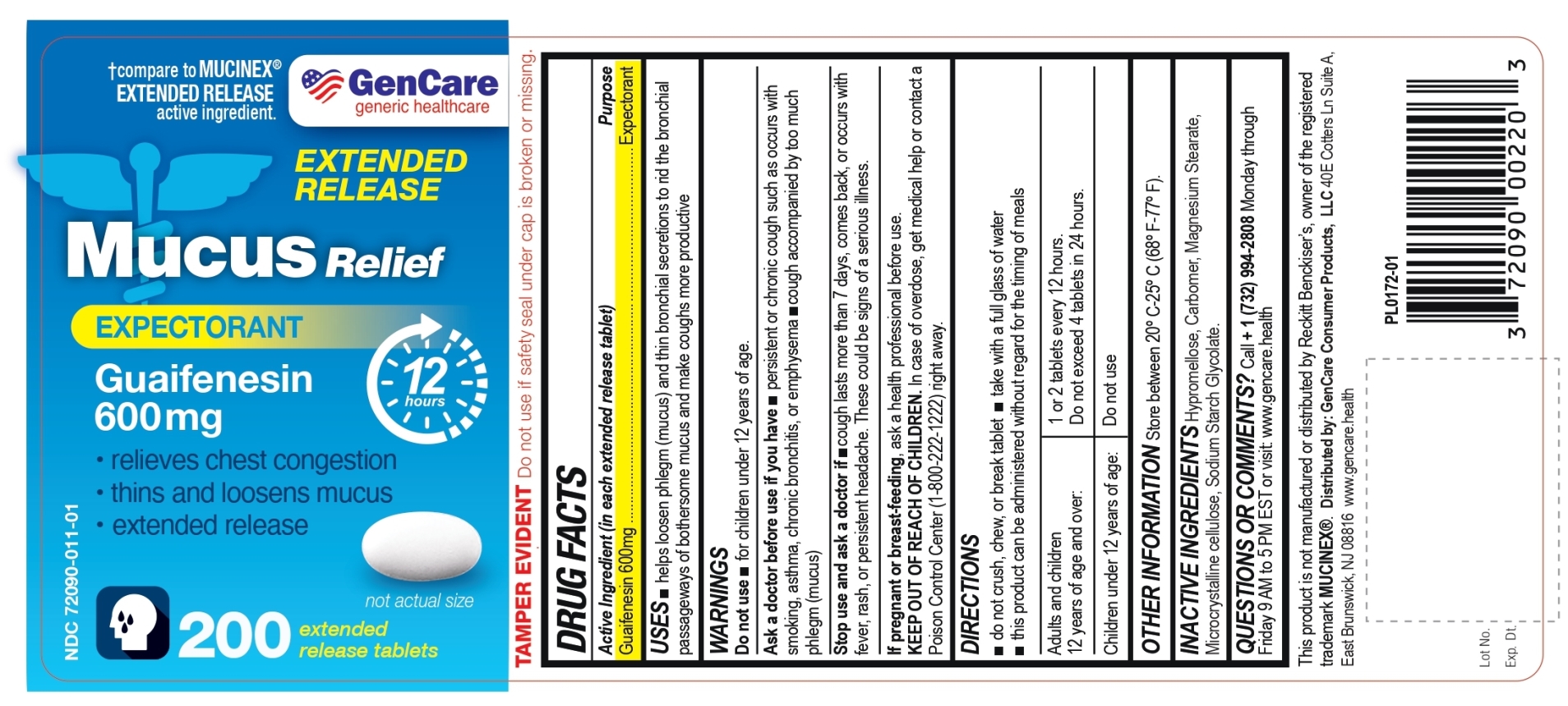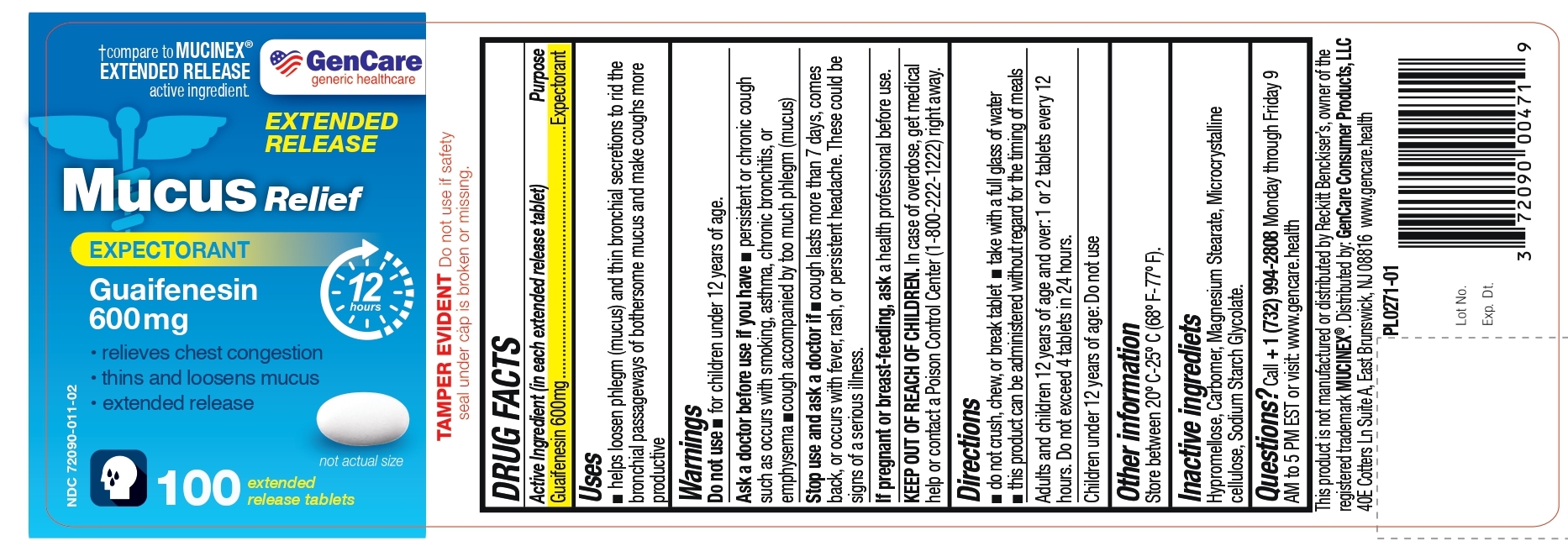 DRUG LABEL: Mucus Relief
NDC: 72090-011 | Form: TABLET, EXTENDED RELEASE
Manufacturer: Pioneer Life Sciences, LLC
Category: otc | Type: HUMAN OTC DRUG LABEL
Date: 20251222

ACTIVE INGREDIENTS: GUAIFENESIN 600 mg/1 1
INACTIVE INGREDIENTS: CARBOMER HOMOPOLYMER TYPE B (ALLYL PENTAERYTHRITOL OR ALLYL SUCROSE CROSSLINKED); HYPROMELLOSE, UNSPECIFIED; MAGNESIUM STEARATE; MICROCRYSTALLINE CELLULOSE; SODIUM STARCH GLYCOLATE TYPE A POTATO

Gencare Mucus Relief Guaifenesin 600mg

Active ingredient (in each extended-release tablet)

Guaifenesin 600 mg

Purpose

Expectorant

Uses

•helps loosen phlegm (mucus) and thin bronchial secretions to rid the bronchial passageways of bothersome mucus and make coughs more productive

Warnings

Do not use

• for children under 12 years of age

Ask a doctor before use if you have

•persistent or chronic cough such as occurs with smoking, asthma, chronic bronchitis, or emphysema

•cough accompanied by too much phlegm (mucus)

Stop use and ask a doctor if

•cough lasts more than 7 days, comes back, or occurs with fever, rash, or persistent headache.

These could be signs of a serious illness.

If pregnant or breast-feeding,

ask a health professional before use.

KEEP OUT OF REACH OF CHILDREN

In case of overdose, get medical help or contact a Poison Control Center right away (1-800-222-1222) right away.

Directions

• do not crush, chew, or break tablet
• take with a full glass of water
• this product can be administered without regard for the timing of meals
• adults and children 12 years of age and over: 1 or 2 tablets every 12 hours. Do not exceed 4 tablets in 24 hours
• children under 12 years of age: do not use

Other information

• store between 20°-25°C (68°-77°F)

Inactive ingredients

Hypromellose, Carbomer, Magnesium Stearate, Microcrystalline cellulose, Sodium Starch Glycolate.

Questions ?

Call + 1 (732) 994-2808 Monday through Friday 9 AM to 5 PM EST or visit: www.gencare.health